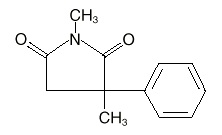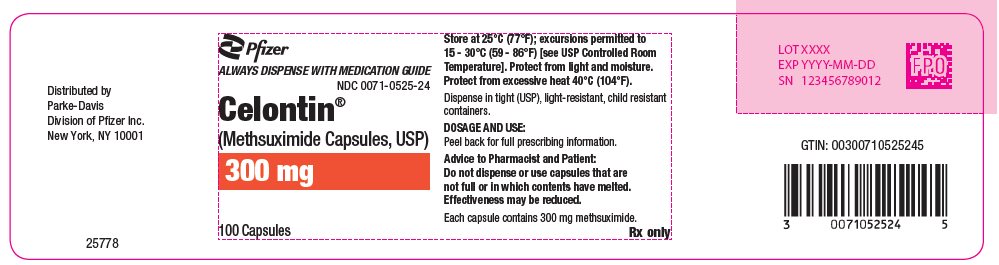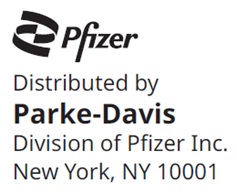 DRUG LABEL: Celontin
NDC: 0071-0525 | Form: CAPSULE
Manufacturer: Parke-Davis Div of Pfizer Inc
Category: prescription | Type: HUMAN PRESCRIPTION DRUG LABEL
Date: 20250129

ACTIVE INGREDIENTS: METHSUXIMIDE 300 mg/1 1
INACTIVE INGREDIENTS: SILICON DIOXIDE; D&C YELLOW NO. 10; FD&C YELLOW NO. 6; GELATIN, UNSPECIFIED; SODIUM LAURYL SULFATE; STARCH, CORN

Celontin®
(Methsuximide Capsules, USP)

DESCRIPTION

Celontin (methsuximide) is an anticonvulsant succinimide, chemically designated as N,2-Dimethyl-2-phenylsuccinimide, with the following structural formula:

Each Celontin capsule contains 300 mg methsuximide, USP. Also contains starch, NF. The capsule contains colloidal silicon dioxide, NF; D&C yellow No. 10; FD&C yellow No. 6; gelatin, NF; and sodium lauryl sulfate, NF.

CLINICAL PHARMACOLOGY

Methsuximide suppresses the paroxysmal three cycle per second spike and wave activity associated with lapses of consciousness which is common in absence (petit mal) seizures. The frequency of epileptiform attacks is reduced, apparently by depression of the motor cortex and elevation of the threshold of the central nervous system to convulsive stimuli.

INDICATIONS AND USAGE

Celontin is indicated for the control of absence (petit mal) seizures that are refractory to other drugs.

CONTRAINDICATIONS

Methsuximide should not be used in patients with a history of hypersensitivity to succinimides.

WARNINGS

Blood dyscrasias

Blood dyscrasias, including some with fatal outcome, have been reported to be associated with the use of succinimides; therefore, periodic blood counts should be performed. Should signs and/or symptoms of infection (eg, sore throat, fever) develop, blood counts should be considered at that point.

Effects on Liver

It has been reported that succinimides have produced morphological and functional changes in animal liver. For this reason, methsuximide should be administered with extreme caution to patients with known liver or renal disease. Periodic urinalysis and liver function studies are advised for all patients receiving the drug.

Systemic Lupus Erythematosus

Cases of systemic lupus erythematosus have been reported with the use of succinimides. The physician should be alert to this possibility.

Suicidal Behavior and Ideation

Antiepileptic drugs (AEDs), including Celontin, increase the risk of suicidal thoughts or behavior in patients taking these drugs for any indication. Patients treated with any AED for any indication should be monitored for the emergence or worsening of depression, suicidal thoughts or behavior, and/or any unusual changes in mood or behavior.

Pooled analyses of 199 placebo-controlled clinical trials (mono- and adjunctive therapy) of 11 different AEDs showed that patients randomized to one of the AEDs had approximately twice the risk (adjusted Relative Risk 1.8, 95% CI:1.2, 2.7) of suicidal thinking or behavior compared to patients randomized to placebo. In these trials, which had a median treatment duration of 12 weeks, the estimated incidence rate of suicidal behavior or ideation among 27,863 AED-treated patients was 0.43%, compared to 0.24% among 16,029 placebo-treated patients, representing an increase of approximately one case of suicidal thinking or behavior for every 530 patients treated. There were four suicides in drug-treated patients in the trials and none in placebo-treated patients, but the number is too small to allow any conclusion about drug effect on suicide.

The increased risk of suicidal thoughts or behavior with AEDs was observed as early as one week after starting drug treatment with AEDs and persisted for the duration of treatment assessed. Because most trials included in the analysis did not extend beyond 24 weeks, the risk of suicidal thoughts or behavior beyond 24 weeks could not be assessed.

The risk of suicidal thoughts or behavior was generally consistent among drugs in the data analyzed. The finding of increased risk with AEDs of varying mechanisms of action and across a range of indications suggests that the risk applies to all AEDs used for any indication. The risk did not vary substantially by age (5–100 years) in the clinical trials analyzed.

Table 1 shows absolute and relative risk by indication for all evaluated AEDs.

Table 1 Risk by indication for antiepileptic drugs in the pooled analysis
Indication | Placebo Patients with Events Per 1000 Patients | Drug Patients with Events Per 1000 Patients | Relative Risk: Incidence of Events in Drug Patients/Incidence in Placebo Patients | Risk Difference: Additional Drug Patients with Events Per 1000 Patients
Epilepsy | 1.0 | 3.4 | 3.5 | 2.4
Psychiatric | 5.7 | 8.5 | 1.5 | 2.9
Other | 1.0 | 1.8 | 1.9 | 0.9
Total | 2.4 | 4.3 | 1.8 | 1.9

The relative risk for suicidal thoughts or behavior was higher in clinical trials for epilepsy than in clinical trials for psychiatric or other conditions, but the absolute risk differences were similar for the epilepsy and psychiatric indications.

Anyone considering prescribing Celontin or any other AED must balance the risk of suicidal thoughts or behavior with the risk of untreated illness. Epilepsy and many other illnesses for which AEDs are prescribed are themselves associated with morbidity and mortality and an increased risk of suicidal thoughts and behavior. Should suicidal thoughts and behavior emerge during treatment, the prescriber needs to consider whether the emergence of these symptoms in any given patient may be related to the illness being treated.

Patients, their caregivers, and families should be informed that AEDs increase the risk of suicidal thoughts and behavior and should be advised of the need to be alert for the emergence or worsening of the signs and symptoms of depression, any unusual changes in mood or behavior, or the emergence of suicidal thoughts, behavior, or thoughts about self-harm. Behaviors of concern should be reported immediately to healthcare providers.

Usage in Pregnancy

Reports suggest an association between the use of anticonvulsant drugs by women with epilepsy and an elevated incidence of birth defects in children born to these women. Data are more extensive with respect to phenytoin and phenobarbital, but these are also the most commonly prescribed anticonvulsants; less systematic or anecdotal reports suggest a possible similar association with the use of all known anticonvulsant drugs.

The reports suggesting an elevated incidence of birth defects in children of drug-treated epileptic women cannot be regarded as adequate to prove a definite cause and effect relationship. There are intrinsic methodologic problems in obtaining adequate data on drug teratogenicity in humans; the possibility also exists that other factors, eg, genetic factors or the epileptic condition itself, may be more important than drug therapy in leading to birth defects. The great majority of mothers on anticonvulsant medication deliver normal infants. It is important to note that anticonvulsant drugs should not be discontinued in patients in whom the drug is administered to prevent major seizures because of the strong possibility of precipitating status epilepticus with attendant hypoxia and threat to life. In individual cases where the severity and frequency of the seizure disorder are such that the removal of medication does not pose a serious threat to the patient, discontinuation of the drug may be considered prior to and during pregnancy, although it cannot be said with any confidence that even minor seizures do not pose some hazard to the developing embryo or fetus.

The prescribing physician will wish to weigh these considerations in treating or counseling epileptic women of childbearing potential.

PRECAUTIONS

General

It is recommended that the physician withdraw the drug slowly on the appearance of unusual depression, aggressiveness, or other behavioral alterations.

As with other anticonvulsants, it is important to proceed slowly when increasing or decreasing dosage, as well as when adding or eliminating other medication. Abrupt withdrawal of anticonvulsant medication may precipitate absence (petit mal) status.

Methsuximide, when used alone in mixed types of epilepsy, may increase the frequency of grand mal seizures in some patients.

Information for Patients

Inform patients of the availability of a Medication Guide, and instruct them to read the Medication Guide prior to taking Celontin. Instruct patients to take Celontin only as prescribed.

Methsuximide may impair the mental and/or physical abilities required for the performance of potentially hazardous tasks, such as driving a motor vehicle or other such activity requiring alertness; therefore, the patient should be cautioned accordingly. Patients taking methsuximide should be advised of the importance of adhering strictly to the prescribed dosage regimen.

Patients should be instructed to promptly contact their physician if they develop signs and/or symptoms suggesting an infection (eg, sore throat, fever).

ADVICE TO THE PHARMACIST AND PATIENT: Since methsuximide has a relatively low melting temperature (124° F), storage conditions which may promote high temperatures (closed cars, delivery vans, or storage near steam pipes) should be avoided. Do not dispense or use capsules that are not full or in which contents have melted. Effectiveness may be reduced. Protect from excessive heat (104° F).

Patients, their caregivers, and families should be counseled that AEDs, including Celontin, may increase the risk of suicidal thoughts and behavior and should be advised of the need to be alert for the emergence or worsening of symptoms of depression, any unusual changes in mood or behavior, or the emergence of suicidal thoughts, behavior, or thoughts about self-harm. Behaviors of concern should be reported immediately to healthcare providers.

Patients should be encouraged to enroll in the North American Antiepileptic Drug (NAAED) Pregnancy Registry if they become pregnant. This registry is collecting information about the safety of antiepileptic drugs during pregnancy. To enroll, patients can call the toll free number 1-888-233-2334 (see PRECAUTIONS: Pregnancy section).

Drug Interactions

Since Celontin (methsuximide) may interact with concurrently administered antiepileptic drugs, periodic serum level determinations of these drugs may be necessary (eg, methsuximide may increase the plasma concentrations of phenytoin and phenobarbital).

Pregnancy

To provide information regarding the effects of in utero exposure to Celontin, physicians are advised to recommend that pregnant patients taking Celontin enroll in the (NAAED) Pregnancy Registry. This can be done by calling the toll free number 1‑888‑233‑2334, and must be done by patients themselves. Information on the registry can also be found at the website:
https://www.aedpregnancyregistry.org/.

See WARNINGS.

Pediatric Use

See DOSAGE AND ADMINISTRATION.

ADVERSE REACTIONS

Gastrointestinal System: Gastrointestinal symptoms occur frequently and have included nausea or vomiting, anorexia, diarrhea, weight loss, epigastric and abdominal pain, and constipation.

Hemopoietic System: Hemopoietic complications associated with the administration of methsuximide have included eosinophilia, leukopenia, monocytosis, and pancytopenia with or without bone marrow suppression.

Nervous System: Neurologic and sensory reactions reported during therapy with methsuximide have included drowsiness, ataxia or dizziness, irritability and nervousness, headache, blurred vision, photophobia, hiccups, and insomnia. Drowsiness, ataxia, and dizziness have been the most frequent side effects noted. Psychologic abnormalities have included confusion, instability, mental slowness, depression, hypochondriacal behavior, and aggressiveness. There have been rare reports of psychosis, suicidal behavior, and auditory hallucinations.

Integumentary System: Dermatologic manifestations which have occurred with the administration of methsuximide have included urticaria, Stevens-Johnson syndrome, and pruritic erythematous rashes.

Cardiovascular: Hyperemia.

Genitourinary System: Proteinuria, microscopic hematuria.

Body as a Whole: Periorbital edema.

OVERDOSAGE

Acute overdoses may produce nausea, vomiting, and CNS depression including coma with respiratory depression. Methsuximide poisoning may follow a biphasic course. Following an initial comatose state, patients have awakened and then relapsed into a coma within 24 hours. It is believed that an active metabolite of methsuximide, N-desmethylmethsuximide, is responsible for this biphasic profile. It is important to follow plasma levels of N-desmethylmethsuximide in methsuximide poisonings. Levels greater than 40 µg/mL have caused toxicity, and coma has been seen at levels of 150 µg/mL.

Treatment

Treatment should include emesis (unless the patient is or could rapidly become obtunded, comatose, or convulsing) or gastric lavage, activated charcoal, cathartics, and general supportive measures. Charcoal hemoperfusion may be useful in removing the N-desmethyl metabolite of methsuximide. Forced diuresis and exchange transfusions are ineffective.

DOSAGE AND ADMINISTRATION

Optimum dosage of Celontin must be determined by trial. A suggested dosage schedule is 300 mg per day for the first week. If required, dosage may be increased thereafter at weekly intervals by 300 mg per day for the three weeks following to a daily dosage of 1.2 g. Because therapeutic effect and tolerance vary among patients, therapy with Celontin must be individualized according to the response of each patient. Optimal dosage is that amount of Celontin which is barely sufficient to control seizures so that side effects may be kept to a minimum.

Celontin may be administered in combination with other anticonvulsants when other forms of epilepsy coexist with absence (petit mal).

HOW SUPPLIED

N 0071-0525-24 (P-D 525)–Celontin Capsules, #1 capsule each containing 300 mg methsuximide; bottles of 100.

STORAGE AND HANDLING

Store at 25°C (77°F); excursions permitted to 15–30°C (59–86°F) [see USP Controlled Room Temperature].

Protect from light and moisture. Protect from excessive heat 40°C (104°F).

LAB-0156-7.0
Revised March 2023

MEDICATION GUIDE

CELONTIN (Suh lŏn' tĭn)
(methsuximide)

Capsules

Read this Medication Guide before you start taking CELONTIN and each time you get a refill. There may be new information. This information does not take the place of talking to your healthcare provider about your medical condition or treatment. If you have any questions about CELONTIN, ask your healthcare provider or pharmacist.

What is the most important information I should know about CELONTIN?

Do not stop taking CELONTIN without first talking to your healthcare provider. Stopping CELONTIN suddenly can cause serious problems.

CELONTIN can cause serious side effects, including:

1. Rare but serious blood problems that may be life-threatening. Call your healthcare provider right away if you have:
  1. fever, swollen glands, or sore throat that come and go or do not go away
  2. frequent infections or an infection that does not go away
  3. easy bruising
  4. red or purple spots on your body
  5. bleeding gums or nose bleeds
  6. severe fatigue or weakness
2. Systematic Lupus Erythematosus. Call your healthcare provider right away if you have any of these symptoms:
  1. joint pain and swelling
  2. muscle pain
  3. fatigue
  4. low-grade fever
  5. pain in the chest that is worse with breathing
  6. unexplained skin rash
3. Like other antiepileptic drugs, CELONTIN may cause suicidal thoughts or actions in a very small number of people, about 1 in 500.
  Call a healthcare provider right away if you have any of these symptoms, especially if they are new, worse, or worry you:
  - thoughts about suicide or dying
  - attempts to commit suicide
  - new or worse depression
  - new or worse anxiety
  - feeling agitated or restless
  - panic attacks
  - trouble sleeping (insomnia)
  - new or worse irritability
  - acting aggressive, being angry, or violent
  - acting on dangerous impulses
  - an extreme increase in activity and talking (mania)
  - other unusual changes in behavior or mood
How can I watch for early symptoms of suicidal thoughts and actions?
  1. Pay attention to any changes, especially sudden changes, in mood, behaviors, thoughts, or feelings.
  2. Keep all follow-up visits with your healthcare provider as scheduled.
Call your healthcare provider between visits as needed, especially if you are worried about symptoms.
Do not stop CELONTIN without first talking to a healthcare provider.
Stopping CELONTIN suddenly can cause serious problems. Stopping a seizure medicine suddenly in a patient who has epilepsy can cause seizures that will not stop (status epilepticus).
Suicidal thoughts or actions can be caused by things other than medicines. If you have suicidal thoughts or actions, your healthcare provider may check for other causes.

What is CELONTIN?

CELONTIN is a prescription medicine used to treat absence (petit mal) seizures that have not gotten better with other seizure medicines.

Who should not take CELONTIN?

Do not take CELONTIN if you are allergic to succinimides (methsuximide or ethosuximide) or any of the ingredients in CELONTIN. See the end of this Medication Guide for a complete list of ingredients in CELONTIN.

What should I tell my healthcare provider before taking CELONTIN?

Before you take CELONTIN, tell your healthcare provider if you:

- have or have had liver problems
- have or have had depression, mood problems or suicidal thoughts or behavior
- have any other medical conditions
- are pregnant or plan to become pregnant. It is not known if CELONTIN can harm your unborn baby. Tell your healthcare provider right away if you become pregnant while taking CELONTIN. You and your healthcare provider will decide if you should take CELONTIN while you are pregnant.
  - If you become pregnant while taking CELONTIN, talk to your healthcare provider about registering with the North American Antiepileptic Drug (NAAED) Pregnancy Registry. The purpose of this registry is to collect information about the safety of antiepileptic drugs during pregnancy. You can enroll in this registry by calling 1‑888‑233‑2334.
- are breastfeeding or plan to breastfeed. It is not known if CELONTIN can pass into breast milk. You and your healthcare provider should decide how you will feed your baby while you take CELONTIN.

Tell your healthcare provider about all the medicines you take, including prescription and non-prescription medicines, vitamins, and herbal supplements. Taking CELONTIN with certain other medicines can cause side effects or affect how well they work. Do not start or stop other medicines without talking to your healthcare provider.

Know the medicines you take. Keep a list of them with you to show your healthcare provider and pharmacist each time you get a new medicine.

How should I take CELONTIN?

- Take CELONTIN exactly as prescribed. Your healthcare provider will tell you how much CELONTIN to take.
- Your healthcare provider may change your dose. Do not change your dose of CELONTIN without talking to your healthcare provider.
- If you take too much CELONTIN, call your healthcare provider or your local Poison Control Center right away.

What should I avoid while taking CELONTIN?

- Do not drink alcohol or take other medicines that make you sleepy or dizzy while taking CELONTIN without first discussing this with your healthcare provider. CELONTIN taken with alcohol or medicines that cause sleepiness or dizziness may make your sleepiness or dizziness worse.
- Do not drive, operate heavy machinery, or do other dangerous activities until you know how CELONTIN affects you. CELONTIN can slow your thinking and motor skills.

What are the possible side effects of CELONTIN?

- See "What is the most important information I should know about CELONTIN?"

CELONTIN may cause other serious side effects, including:

- Grand mal seizures can happen more often or become worse

The most common side effects of CELONTIN include:

- drowsiness
- dizziness
- headache
- blurred vision
- nausea or vomiting
- constipation

- diarrhea
- weight loss
- problems with walking and coordination (unsteadiness)
- stomach pain
- loss of appetite

Tell your healthcare provider about any side effect that bothers you or that does not go away.

These are not all the possible side effects with CELONTIN. For more information, ask your healthcare provider or pharmacist.

Call your doctor for medical advice about side effects. You may report side effects to FDA at 1‑800‑FDA‑1088.

How should I store CELONTIN?

- Store CELONTIN at room temperature, between 59°F to 86°F (15°C to 30°C).
- Keep CELONTIN capsules in a dry place.
- Keep CELONTIN out of the light.
- Protect CELONTIN from heat.
- Do not use CELONTIN capsules that if they do not look full or if the contents have melted.

Keep CELONTIN and all medicines out of the reach of children.

General information about CELONTIN

Medicines are sometimes prescribed for purposes other than those listed in a Medication Guide. Do not use CELONTIN for a condition for which it was not prescribed. Do not give CELONTIN to other people, even if they have the same condition. It may harm them.

This Medication Guide summarizes the most important information about CELONTIN. If you would like more information, talk with your healthcare provider. You can ask your healthcare provider or pharmacist for information about CELONTIN that is written for healthcare professionals.

For more information, go to www.pfizer.com or call 1-800-438-1985.

What are the ingredients in CELONTIN?

Active ingredient: methsuximide

Inactive ingredients: starch, colloidal silicon dioxide NF, D&C yellow No. 10, FD&C yellow No.6, gelatin NF, and sodium lauryl sulfate NF.

This Medication Guide has been approved by the U.S. Food and Drug Administration.

LAB-0404-3.0
Revised March 2023

PRINCIPAL DISPLAY PANEL - 300 mg Capsule Bottle Label

Pfizer

ALWAYS DISPENSE WITH MEDICATION GUIDE
NDC 0071-0525-24

Celontin®
(Methsuximide Capsules, USP)

300 mg

100 Capsules